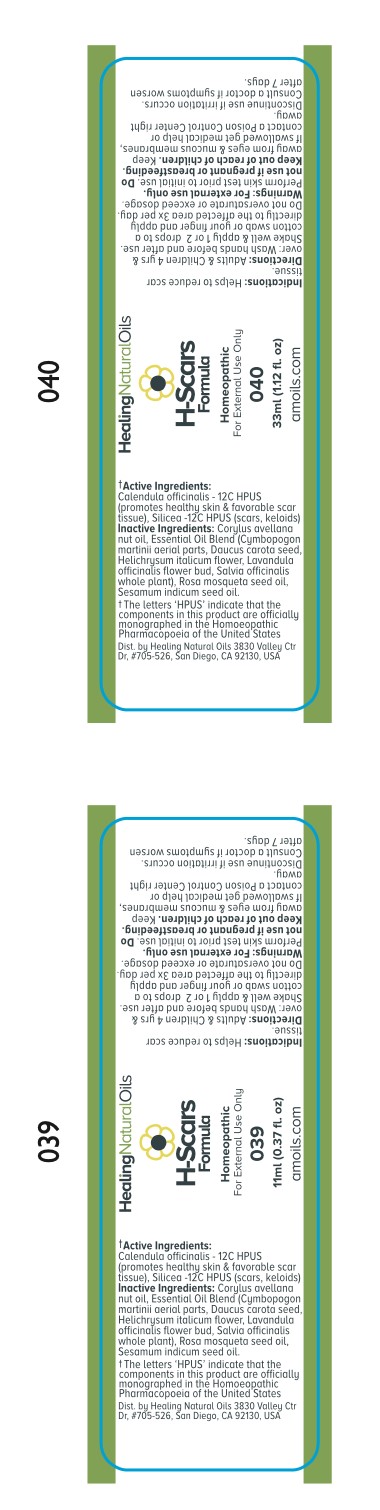 DRUG LABEL: H-Scars Formula
NDC: 61077-039 | Form: OIL
Manufacturer: Healing Natural Oils LLC
Category: homeopathic | Type: HUMAN OTC DRUG LABEL
Date: 20250408

ACTIVE INGREDIENTS: CALENDULA OFFICINALIS FLOWERING TOP 12 [hp_C]/11 mL; SILICON DIOXIDE 12 [hp_C]/11 mL
INACTIVE INGREDIENTS: SESAME OIL; EUROPEAN HAZELNUT OIL; CYMBOPOGON MARTINI TOP; DAUCUS CAROTA SUBSP. SATIVUS SEED; HELICHRYSUM ITALICUM FLOWER; LAVANDULA ANGUSTIFOLIA FLOWERING TOP; SALVIA OFFICINALIS WHOLE; JOJOBA OIL

Active Ingredients:

Calendula officinalis -12C HPUS

Silicea - 12C HPUS

Purpose

Calendula officinalis - 12C HPUS (promotes healthy skin and favorable scar tissue)

Silicea - 12C HPUS (scars, keloids)

The letters ‘HPUS’ indicate that the components in this product are officially
monographed in the Homoeopathic Pharmacopoeia of the United States

Inactive Ingredients:

Corylus avellana nut oil, Essential Oil Blend (Cymbopogon martinii aerial parts, Daucus carota seed, Helichrysum italicum flower, Lavandula officinalis flower bud, Salvia officinalis whole plant), Rosa mosqueta seed oil, Sesamum indicum seed oil.

Indications:

Helps to reduce scar tissue

Directions:

Adults and Children 4 yrs and over: Wash hands before and after use.
Shake well and apply 1 or 2 drops to a cotton swab or your finger and apply directly to the affected area 3x per day.
Do not oversaturate or exceed dosage.

Warnings:

For external use only.
Perform skin test prior to initial use.

Do not use if pregnant or breastfeeding.

Keep out of reach of children.

OTHER SAFETY INFORMATION

Keep away from eyes and mucous membranes. If swallowed get medical help or contact a Poison Control
Center right away.

Discontinue use if irritation occurs.

ASK DOCTOR

Consult a doctor if symptoms worsen after 7 days.

DESCRIPTION

Dist. by Healing Natural Oils 3830 Valley Ctr Dr, #705-526, San Diego, CA 92130, USA

PACKAGE LABEL

Healing Natural Oils
H- Scars
Formula

Homeopathic

For External Use Only

039

11ml (0.37 fl. oz)
amoils.com